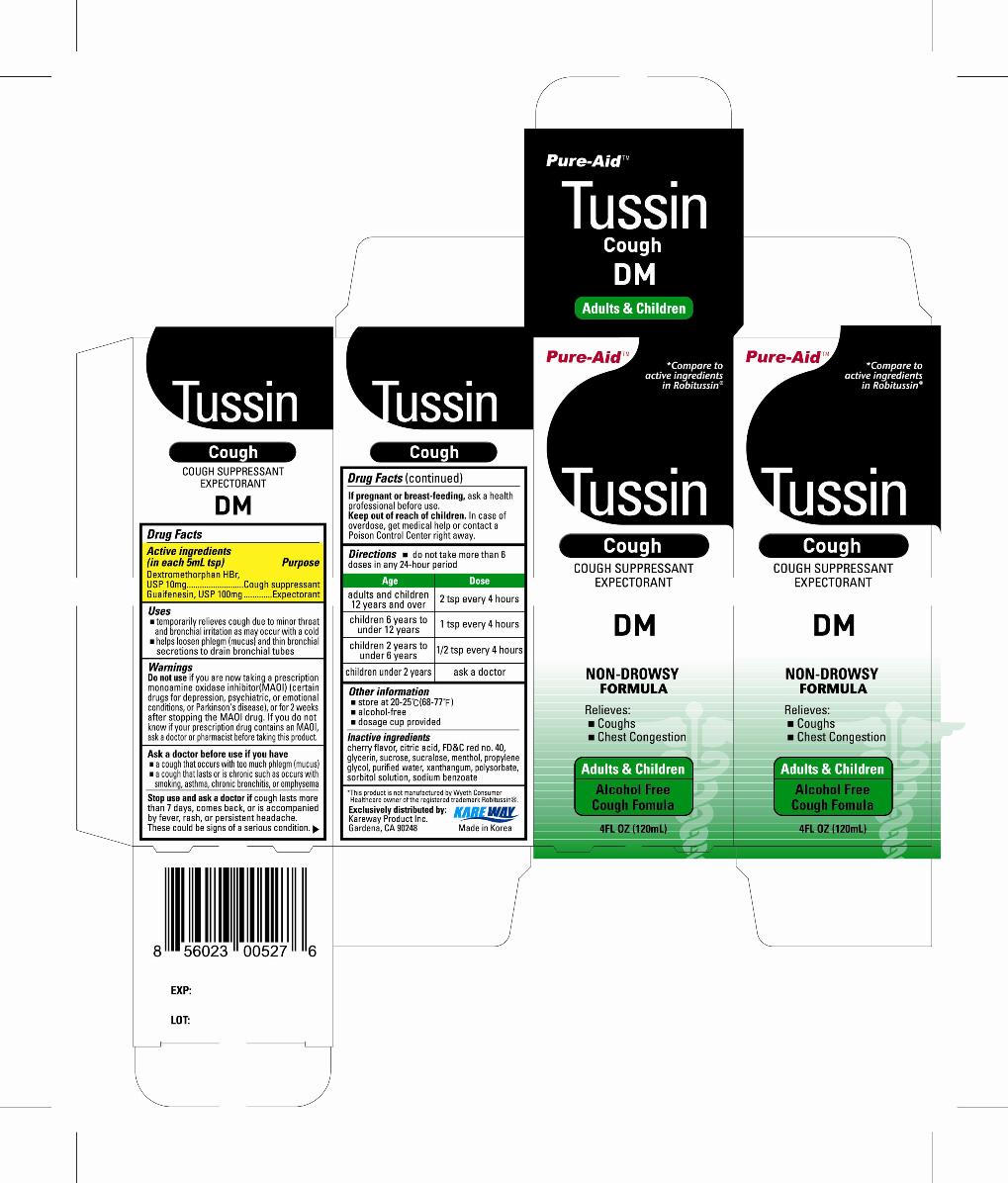 DRUG LABEL: Tussin DM
NDC: 67510-0527 | Form: LIQUID
Manufacturer: Kareway Product, Inc.
Category: otc | Type: HUMAN OTC DRUG LABEL
Date: 20110826

ACTIVE INGREDIENTS: DEXTROMETHORPHAN HYDROBROMIDE 10 mg/5 mL; GUAIFENESIN 100 mg/5 mL
INACTIVE INGREDIENTS: CHERRY; CITRIC ACID MONOHYDRATE; FD&C RED NO. 40; GLYCERIN; SUCROSE; SUCRALOSE; MENTHOL; PROPYLENE GLYCOL; WATER; XANTHAN GUM; POLYSORBATE 20; SORBITOL; SODIUM BENZOATE

Drug Facts

Active ingredients

(in each 5mL tsp)

Dextromethorphan HBr, USP 10mg

Guaifenesin, USP 100mg

Purpose

Cough suppressant

Expectorant

Uses

- temporarily relieves cough due to minor throat and bronchial irritation as may occur with a cold
- helps loosen phlegm (mucus) and thin bronchial secretions to drain bronchial tubes

Warnings

Do not use

if you are now taking a prescription monoamine oxidase inhibitor (MAOI) (certain drugs for depression, psychiatric, or emotional conditions, or Parkinson's disease), or for 2 weeks after stopping the MAOI drug. If you do not know if your prescription drug contains an MAOI, ask a doctor or pharmacist before taking this product.

Ask a doctor before use if you have

- a cough that occurs with too much phlegm (mucus)
- a cough that lasts or is chronic such as occurs with smoking, asthma, chronic bronchitis, or emphysema

Stop use and ask a doctor ir

cough lasts more than 7 days, comes back, or is accompanied by fever, rash, or persistent headache. These could be signs of a serious condition.

If pregnant or breast-feeding,

ask a health professional before use.

Keep out of reach of children.

In case of overdose, get medical help or contact a Poison Control Center right away.

Directions

- do not take more than 6 doses in any 24-hour period

Age | Dose
adults and children 12 years and over | 2 tsp every 4 hours
children 6 years to under 12 years | 1 tsp every 4 hours
children 2 years to under 6 years | 1/2 tsp every 4 hours
children under 2 years | ask a doctor

Other information

- store at 20-25°C (68-77°F)
- alcohol-free
- dosage cup provided

Inactive ingredients

cherry flavor, citric acid, FD and C red no. 40, glycerin, sucrose, sucralose, menthol, propylene glycol, purified water, xanthan gum, polysorbate, sorbitol solution, sodium benzoate

Package label

Tussin DM